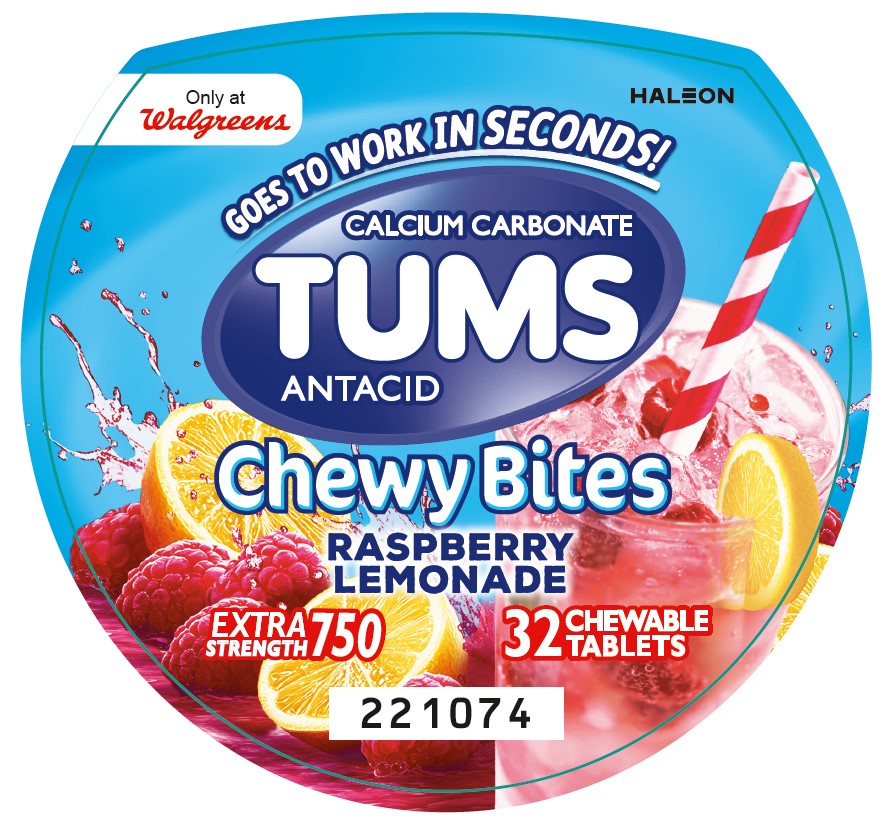 DRUG LABEL: Tums
NDC: 0135-0188 | Form: TABLET, CHEWABLE
Manufacturer: Haleon US Holdings LLC
Category: otc | Type: HUMAN OTC DRUG LABEL
Date: 20260202

ACTIVE INGREDIENTS: CALCIUM CARBONATE 750 mg/1 1
INACTIVE INGREDIENTS: ACACIA; YELLOW WAX; CARMINIC ACID; CARNAUBA WAX; CITRIC ACID MONOHYDRATE; COCONUT OIL; STARCH, CORN; CORN SYRUP; DEXTRIN, CORN; FD&C BLUE NO. 2 ALUMINUM LAKE; FD&C RED NO. 40 ALUMINUM LAKE; FD&C YELLOW NO. 5 ALUMINUM LAKE; MALTODEXTRIN; MEDIUM-CHAIN TRIGLYCERIDES; METHYLPARABEN; PHOSPHORIC ACID; POVIDONE, UNSPECIFIED; PROPYLENE GLYCOL; PROPYLPARABEN; WATER; SHELLAC; SODIUM BENZOATE; SORBIC ACID; SORBITOL; SOYBEAN LECITHIN; SUCROSE; TITANIUM DIOXIDE; TRIACETIN; CORN OIL

Drug Facts

Active ingredient (per tablet)

Calcium carbonate 750 mg

Purpose

Antacid

Uses

relieves

- heartburn
- acid indigestion
- sour stomach
- upset stomach associated with these symptoms

Warnings

Ask a doctor or pharmacist before use if you are

presently taking a prescription drug. Antacids may interact with certain prescription drugs.

When using this product

- do not take more than 6 tablets in 24 hours
- if pregnant do not take more than 6 tablets in 24 hours
- do not use the maximum dosage for more than 2 weeks, except under the advice and supervision of a doctor

Directions

- adults and children 12 years of age and over: chew 2-4 tablets as symptoms occur, or as directed by a doctor. Chew or crush tablets completely before swallowing.
- do not take for symptoms that persist for more than 2 weeks unless advised by a doctor

Other information

- each tablet contains: elemental calcium 300 mg
- do not store above 25°C (77°F)
- contains FD&C Yellow No. 5 (tartrazine) as a color additive

Inactive ingredients

acacia, beeswax, carmine, carnauba wax, citric acid, coconut oil, corn starch, corn syrup, dextrin, FD&C blue no. 2 aluminum lake, FD&C red no. 40 aluminum lake, FD&C yellow no. 5 aluminum lake (tartrazine), maltodextrin, medium-chain triglycerides, methylparaben, natural and artificial flavors, pharmaceutical ink, phosphoric acid, povidone, propylene glycol, propylparaben, purified water, shellac, sodium benzoate, sorbic acid, sorbitol, soy lecithin, sucrose, titanium dioxide, triacetin, vegetable oil

Questions or comments?

1-800-452-0051

Additional Information

Do not use if inner safety seal under cap is broken or missing.

Principal Display Panel

Only at Walgreens

GOES TO WORK IN SECONDS!

CALCIUM CARBONATE

TUMS

ANTACID

Chewy Bites

RASPBERRY LEMONADE

EXTRA STRENGTH 750

32 CHEWABLE TABLETS